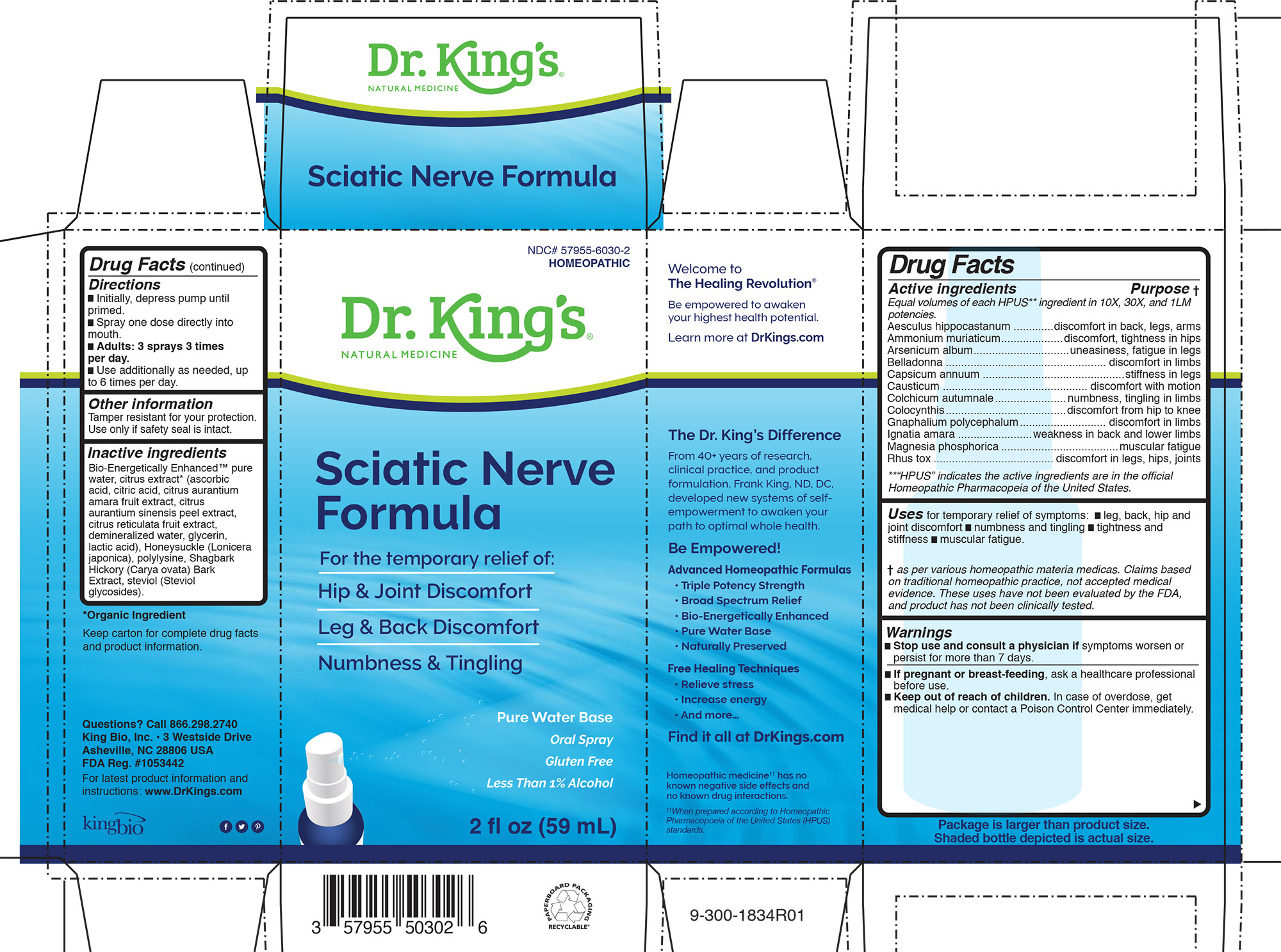 DRUG LABEL: Sciatic Nerve Formula
NDC: 57955-6030 | Form: LIQUID
Manufacturer: King Bio Inc.
Category: homeopathic | Type: HUMAN OTC DRUG LABEL
Date: 20200813

ACTIVE INGREDIENTS: HORSE CHESTNUT 10 [hp_X]/59 mL; AMMONIUM CHLORIDE 10 [hp_X]/59 mL; ARSENIC TRIOXIDE 10 [hp_X]/59 mL; ATROPA BELLADONNA 10 [hp_X]/59 mL; CAPSICUM 10 [hp_X]/59 mL; CAUSTICUM 10 [hp_X]/59 mL; COLCHICUM AUTUMNALE BULB 10 [hp_X]/59 mL; CITRULLUS COLOCYNTHIS FRUIT PULP 10 [hp_X]/59 mL; PSEUDOGNAPHALIUM OBTUSIFOLIUM 10 [hp_X]/59 mL; STRYCHNOS IGNATII SEED 10 [hp_X]/59 mL; MAGNESIUM PHOSPHATE, DIBASIC TRIHYDRATE 10 [hp_X]/59 mL; TOXICODENDRON PUBESCENS LEAF 10 [hp_X]/59 mL
INACTIVE INGREDIENTS: WATER; CARYA OVATA BARK; CITRUS BIOFLAVONOIDS; LONICERA JAPONICA FLOWER; POLYEPSILON-LYSINE (4000 MW); REBAUDIOSIDE A

Sciatic Nerve Formula™

Drug Facts

____________________________________________________________________________________________________________

Equal volumes of each ingredient in 10X, 30X, and LM1 potencies.

HPUS active ingredients: Aesculus hippocastanum, Ammonium muriaticum, Arsenicum album, Belladonna, Capsicum annuum, Causticum, Colchicum autumnale, Colocynthis, Gnaphalium polycephalum, Ignatia amara, Magnesia phosphoria, Rhus toxicodendron .

INDICATIONS AND USAGE

Uses for temporary relief of symptoms: █ leg, back, hip and
joint discomfort █ numbness and tingling █ tightness and
stiffness █ muscular fatigue.

Warnings

█ Stop use and consult a physician if symptoms worsen or
persist for more than 7 days

PREGNANCY OR BREAST FEEDING

If pregnant or breast-feeding, ask a healthcare professional
before use.

Keep out of reach of children. In case of overdose, get
medical help or contact a Poison Control Center immediately.

Directions:

- Initially, depress pump until primed.
- Spray one dose directly into mouth.
- Adults: 3 sprays 3 times per day.
- Use additionally as needed, up to 6 times per day.

Other information
Tamper resistant for your protection.
Use only if safety seal is intact.

Inactive Ingredients

Bio-Energetically Enhanced™ pure
water, citrus extract* (ascorbic
acid, citric acid, citrus aurantium
amara fruit extract, citrus
aurantium sinensis peel extract,
citrus reticulata fruit extract,
demineralized water, glycerin,
lactic acid), Honeysuckle (Lonicera
japonica), polylysine, Shagbark
Hickory (Carya ovata) Bark
Extract, steviol (Steviol
glycosides).

Drug Facts

________________________________________________

Active ingredients Purpose

Equal volumes of each HPUS** ingredient in 10X, 30X, and 1LM
potencies.
Aesculus hippocastanum .............discomfort in back, legs, arms
Ammonium muriaticum....................discomfort, tightness in hips
Arsenicum album...............................uneasiness, fatigue in legs
Belladonna .................................................... discomfort in limbs
Capsicum annuum ..............................................stiffness in legs
Causticum ............................................... discomfort with motion
Colchicum autumnale.......................numbness, tingling in limbs
Colocynthis.......................................discomfort from hip to knee
Gnaphalium polycephalum............................ discomfort in limbs
Ignatia amara ........................weakness in back and lower limbs
Magnesia phosphorica ......................................muscular fatigue
Rhus tox ....................................... discomfort in legs, hips, joints
**“HPUS” indicates the active ingredients are in the official
Homeopathic Pharmacopeia of the United States.

Questions? Call 866.298.2740
King Bio, Inc. • 3 Westside Drive
Asheville, NC 28806 USA
FDA Reg. #1053442

For latest product information and
instructions: www.DrKings.com